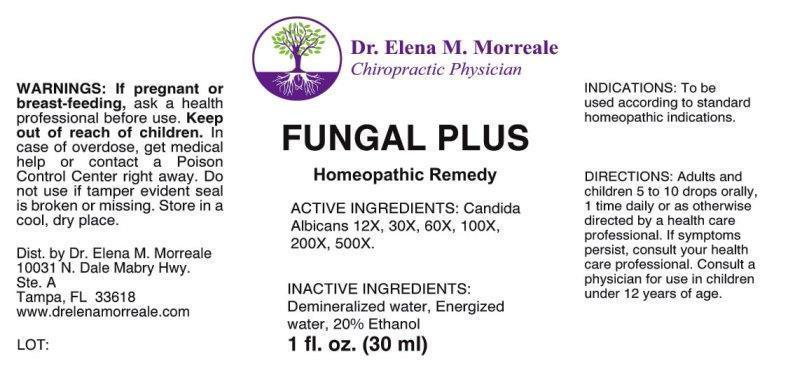 DRUG LABEL: Fungal Plus
NDC: 50813-0008 | Form: LIQUID
Manufacturer: Dr Elena Morreale
Category: homeopathic | Type: HUMAN OTC DRUG LABEL
Date: 20150121

ACTIVE INGREDIENTS: CANDIDA ALBICANS 12 [hp_X]/1 mL
INACTIVE INGREDIENTS: WATER; ALCOHOL

DRUG FACTS:

ACTIVE INGREDIENTS:

Candida Albicans 12X, 30X, 60X, 100X, 200X, 500X

INDICATIONS:

To be used according to standard homeopathic indications.

WARNINGS:

If pregnant or breast-feeding, ask a health care professional before use.

Keep out of reach of children. In case of overdose, get medical help or contact a Poison Control Center right away.

Do not use if tamper evident seal is broken or missing.

Store in cool, dry place.

Keep out of reach of children. In case of overdose, get medical help or contact a Poison Control Center right away.

DIRECTIONS:

Adults and children 5 to 10 drops orally, 1 time daily or as otherwise directed by a health professional. If symptoms persist, consult your health care professional. Consult a physician for use in children under 12 years of age.

INDICATIONS:

To be used according to standard homeopathic indications.

INACTIVE INGREDIENTS:

Demineralized water, Energized water, 20% Ethanol

QUESTIONS:

Dist. by Dr. Elena M. Morreale

10031 N. Dale Mabry Hwy,

Ste. A

Tampa, FL 33618

www.drelenamorreale.com

PACKAGE LABEL DISPLAY

Dr. Elena M. Morreale

Chiropractic Physician

FUNGAL PLUS

Homeopathic Remedy

1 fl. oz. (30 ml)